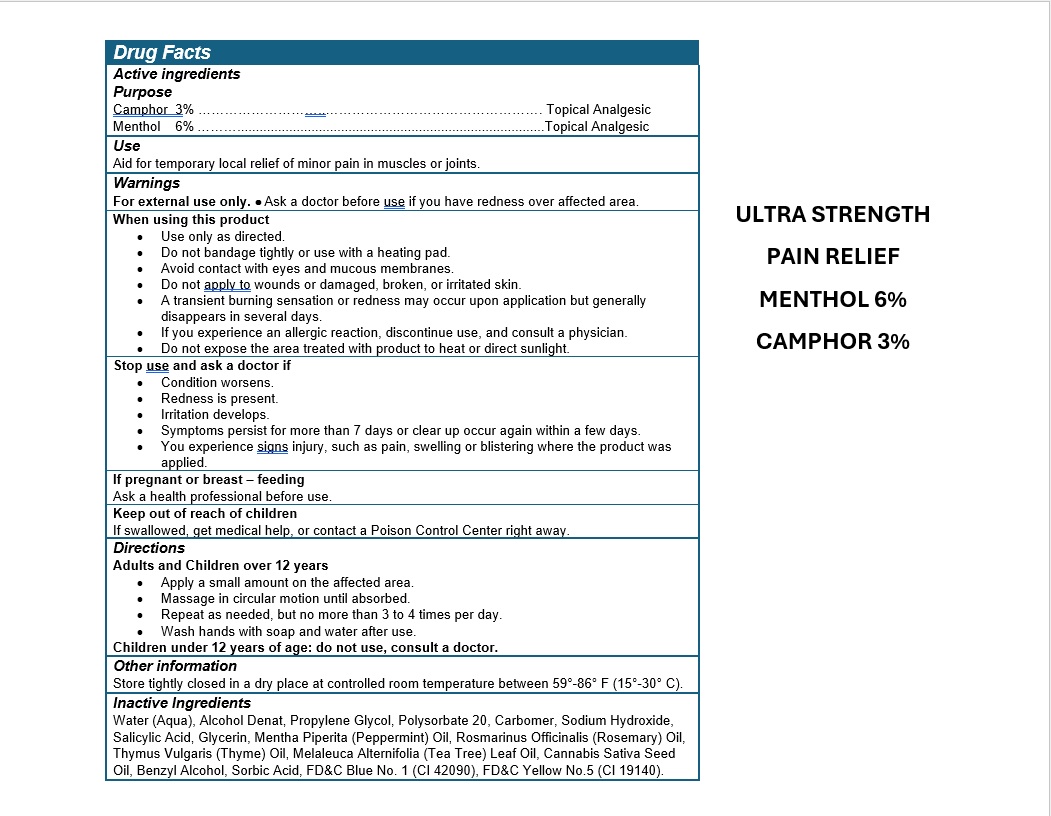 DRUG LABEL: COOLING PAIN RELIEF
NDC: 49283-581 | Form: GEL
Manufacturer: CHEMCO CORPORATION
Category: otc | Type: HUMAN OTC DRUG LABEL
Date: 20260205

ACTIVE INGREDIENTS: MENTHOL 6 g/100 mL; CAMPHOR (SYNTHETIC) 3 g/100 mL
INACTIVE INGREDIENTS: PROPYLENE GLYCOL; MENTHA PIPERITA (PEPPERMINT) OIL; FD&C YELLOW NO. 5; CARBOMER 940; GLYCERIN; SALICYLIC ACID; FD&C BLUE NO. 1; POLYSORBATE 20; ROSEMARY OIL; SORBIC ACID; WATER; BENZYL ALCOHOL; SODIUM HYDROXIDE; THYMUS VULGARIS (THYME) OIL; MELALEUCA ALTERNIFOLIA (TEA TREE) LEAF OIL; CANNABIS SATIVA SEED OIL; ALCOHOL

49283-581-20

ACTIVE INGREDIENT

Menthol 6%

Camphor 3%

PURPOSE

Topical Analgesic

Use

Aid for temporary local relief of minor pain in muscles or joints.

WARNINGS

- For external use only.
- Ask a doctor before use if you have redness over affected area

WHEN USING

- Use only as directed
- Do not bandage tightly or use with a heating pad
- Avoid contact with eyes and mucous membranes
- Do not apply to wounds or damaged, broken, or irritated skin
- A transient burning sensation or redness may occur upon application but generally disappears in several days
- If you experience an allergic reaction, discontinue use, and consult a physician
- Do not expose the area treated with product to heat or direct sunlight.

Stop use and ask a doctor if

- Condition worsens.
- Redness is present
- Irritation develops
- Symptoms persist for more than 7 days or clear up occur again within a few days
- You experience signs injury, such as pain, swelling or blistering where the product was applied.

If pregnant or breast-feeding

Ask a health professional before use.

KEEP OUT OF REACH OF CHILDREN

If swallowed, get medical help or contact a Poison Control Center right away.

Directions

Adults and children over 12 years

- Apply a small amount on the affected area.
- Massage in a circular motion until absorbed, let set for a few seconds.
- Repeat as needed, but no more than 3 to 4 times per day.
- Store tightly closed in a dry place at controlled room temperature between 59°-86° F (15°-30° C).
- Wash hands with soap and water after use.

Children under 12 years of age consult a doctor.

INACTIVE INGREDIENT

Water (Aqua), Alcohol Denat, Propylene Glycol, Polysorbate 20, Carbomer, Sodium Hydroxide, Salicylic Acid, Glycerin, Mentha Piperita (Peppermint) Oil, Rosmarinus Officinalis (Rosemary) Oil, Thymus Vulgaris (Thyme) Oil, Melaleuca Alternifolia (Tea Tree) Leaf Oil, Cannabis Sativa (Hemp) Seed Oil, Benzyl Alcohol, Sorbic Acid, FD&C Blue No. 1 (CI 42090), FD&C Yellow No.5 (CI 19140).